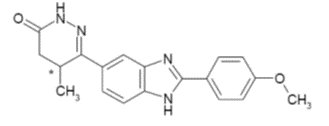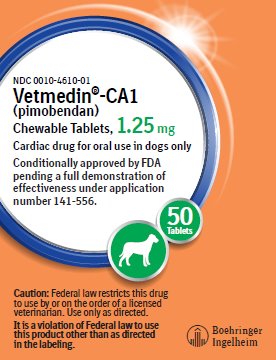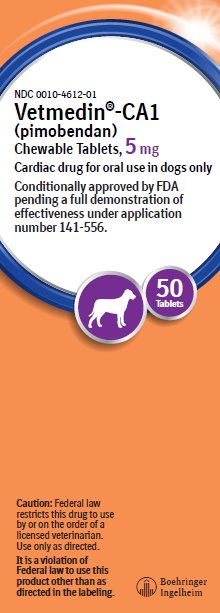 DRUG LABEL: Vetmedin-CA1
NDC: 0010-4610 | Form: TABLET, CHEWABLE
Manufacturer: Boehringer Ingelheim Animal Health USA Inc.
Category: animal | Type: PRESCRIPTION ANIMAL DRUG LABEL
Date: 20240905

ACTIVE INGREDIENTS: PIMOBENDAN 1.25 mg/1 1

Vetmedin®-CA1 (pimobendan)
Chewable Tablets

Cardiac drug for oral use in dogs only

Caution:

Federal law restricts this drug to use by or on the order of a licensed veterinarian. Use only as directed.

It is a violation of Federal law to use this product other than as directed in the labeling.

Conditionally approved by FDA pending a full demonstration of effectiveness under application number 141-556.

Description:

VETMEDIN-CA1 (pimobendan) is supplied as oblong half-scored chewable tablets containing 1.25 or 5 mg pimobendan per tablet. Pimobendan, a benzimidazole-pyridazinone derivative, is a non-sympathomimetic, non-glycoside inotropic drug with vasodilatative properties. Pimobendan exerts a stimulatory myocardial effect by a dual mechanism of action consisting of an increase in calcium sensitivity of cardiac myofilaments and inhibition of phosphodiesterase (Type III). Pimobendan exhibits

vasodilating activity by inhibiting phosphodiesterase III activity. The chemical name of pimobendan is 4,5-dihydro-6-[2-(4-methoxyphenyl)-1H-benzimidazole-5-yl]-5-methyl-3(2H)-pyridazinone. The structural formula of pimobendan is:

Indications:

VETMEDIN-CA1 (pimobendan) is indicated for the delay of onset of congestive heart failure in dogs with Stage B2 preclinical myxomatous mitral valve disease (2019 ACVIM Consensus Statement^1).

Stage B2 preclinical myxomatous mitral valve disease (MMVD) refers to dogs with asymptomatic MMVD that have a moderate or loud mitral murmur due to mitral regurgitation and cardiomegaly.

Dosage and Administration:

Always provide the Client Information Sheet to the dog owner with each prescription. VETMEDIN-CA1 should be administered orally at a total daily dose of 0.23 mg/lb (0.5 mg/kg) body weight, using a suitable combination of whole or half tablets. The total daily dose should be divided into 2 portions that are not necessarily equal, and the portions should be administered approximately 12 hours apart (i.e., morning and evening). The tablets are scored, and the calculated dosage should be provided to the nearest half tablet increment.

Contraindications:

Do not administer VETMEDIN-CA1 in cases of hypertrophic cardiomyopathy, aortic stenosis, or any other clinical condition where an augmentation of cardiac output is inappropriate for functional or anatomical reasons.

Do not administer VETMEDIN-CA1 to dogs with Stage A or B1 preclinical MMVD (2019 ACVIM Consensus Statement) due to the risk of cardiac pathology associated with exaggerated hemodynamic responses to VETMEDIN-CA1.

Warnings:

User Safety Warnings: Not for use in humans. Keep this and all medications out of reach of children. Consult a physician in case of accidental ingestion by humans.

Animal Safety Warnings: Keep VETMEDIN-CA1 in a secure location out of reach of dogs, cats, and other animals to prevent accidental ingestion or overdose.

At 3 and 5 times the recommended dosage, administered over a 6-month period of time, pimobendan caused an exaggerated hemodynamic response in the normal dog heart, which was associated with cardiac pathology (See Target Animal Safety).

Precautions:

For use only in dogs with preclinical MMVD that have a moderate or loud mitral murmur due to mitral regurgitation and cardiomegaly (Stage B2 MMVD, 2019 ACVIM Consensus Statement). A diagnosis of MMVD should be made by means of a comprehensive physical and cardiac examination which should include radiography and echocardiography. Stage B2 cardiomegaly is diagnosed based on meeting all three of the following criteria:

• Radiographic vertebral heart score (VHS) >10.5, and

• Echocardiographic left atrium/aorta ratio (LA/Ao ratio) ≥1.6, and

• Echocardiographic left ventricular internal diastolic diameter normalized to body weight (LVIDDN) ≥1.7.

Echocardiographic examination is recommended in all cases to diagnose MMVD and confirm cardiomegaly. If therapy is initiated prior to the development of cardiomegaly, treated dogs are at risk for cardiac pathology associated with exaggerated hemodynamic responses to VETMEDIN-CA1.

If only radiographic examination is possible, cardiomegaly may be diagnosed in cases where the VHS ≥11.5 and the vertebral left atrial size (VLAS) ≥3.01,2. If radiographic cardiomegaly does not meet both of these criteria, an echocardiogram should be performed prior to the initiation of therapy with VETMEDIN-CA1.

VETMEDIN-CA1 has not been evaluated in dogs receiving concomitant heart medications.

The safety of VETMEDIN-CA1 has not been established in dogs with asymptomatic heart disease caused by etiologies other than MMVD. The safe use of VETMEDIN-CA1 has not been evaluated in dogs younger than 6 months of age, dogs with congenital heart defects, dogs with diabetes mellitus or other serious metabolic diseases, dogs used for breeding, or pregnant or lactating bitches.

Adverse Reactions:

In a controlled multi-center field study, 363 dogs with preclinical MMVD (Stage B2 MMVD, 2019 ACVIM Consensus Statement) received at least one dose of VETMEDIN-CA1 (n=182) or the placebo control chewable tablets (n=181) for up to 1563 days. During this long-term study, dogs were followed until the development of congestive heart failure (CHF). Adverse reactions were seen in both treatment groups with many findings associated with the progression of MMVD and comorbidities consistent with the age of the enrolled dogs.

The median time to the primary endpoint (development of left-sided CHF or cardiac death/euthanasia) was 38% longer in the VETMEDIN-CA1 group. Despite the longer duration on study, the incidence of reported adverse reactions was similar between treatment groups.

Cough was the most frequently reported adverse reaction. This clinical finding is commonly reported in cases of MMVD and the incidence was similar between treatment groups. Lethargy, inappetence, tachypnea, collapse, arrhythmia, and syncope may also be associated with the progression of MMVD and were reported in dogs receiving VETMEDIN-CA1.

Adverse reactions not related to disease progression in dogs receiving VETMEDIN-CA1 included diarrhea, vomiting, pain, lameness, arthritis, urinary tract infection, and seizure.

Mortality rate, regardless of reason, prior to CHF was similar between the VETMEDIN-CA1 and the control groups.

Contact Information: To report suspected adverse reactions, to obtain a Safety Data Sheet (SDS), or for technical assistance, contact Boehringer Ingelheim Animal Health USA Inc. at 1-888-637-4251. For additional information about reporting adverse drug experiences for animal drugs, contact FDA at 1-888-FDA-VETS or at www.fda.gov/reportanimalae.

Information for Dog Owners:

Always provide the Client Information Sheet with each prescription and review it with the dog owner or person responsible for care of the dog. Advise dog owners about signs of disease progression and possible adverse reactions with use of VETMEDIN-CA1.

Clinical Pharmacology:

Pimobendan is oxidatively demethylated to a pharmacologically active metabolite which is then conjugated with sulfate or glucuronic acid and excreted mainly via feces. The mean extent of protein binding of pimobendan and the active metabolite in dog plasma is >90%. Following a single oral administration of 0.25 mg/kg VETMEDIN-CA1, the maximal mean (± 1 SD) plasma concentrations (Cmax) of pimobendan and the active metabolite were 3.09 (0.76) ng/mL and 3.66 (1.21) ng/mL, respectively. Individual dog Cmax values for pimobendan and the active metabolite were observed 1 to 4 hours post-dose (mean: 2 and 3 hours, respectively). The total body clearance of pimobendan was approximately 90 mL/min/kg, and the terminal elimination half-lives of pimobendan and the active metabolite were approximately 0.5 hours and 2 hours, respectively.

Plasma levels of pimobendan and active metabolite were below quantifiable levels by 4 and 8 hours after oral administration, respectively. The steady-state volume of distribution of pimobendan is 2.6 L/kg indicating that the drug is readily distributed into tissues. Food decreased the bioavailability of an aqueous solution of pimobendan, but the effect of food on the absorption of pimobendan from VETMEDIN-CA1 is unknown.

In normal dogs instrumented with left ventricular (LV) pressure transducers, pimobendan increased LV dP/dtmax (a measure of contractility of the heart) in a dose dependent manner between 0.1 and 0.5 mg/kg orally. The effect was still present 8 hours after dosing. There was a delay between peak blood levels of pimobendan and active metabolite and the maximum physiologic response (peak LV dP/dtmax). Blood levels of pimobendan and active metabolite began to drop before maximum contractility was seen. Repeated oral administration of pimobendan did not result in evidence of tachyphylaxis (decreased positive inotropic effect) or drug accumulation (increased positive inotropic effect). Laboratory studies indicate that the positive inotropic effect of pimobendan may be attenuated by the concurrent use of a β-adrenergic blocker or a calcium channel blocker.

Reasonable Expectation of Effectiveness:

A reasonable expectation of effectiveness may be demonstrated based on evidence such as, but not limited to, pilot data in the target species or studies from published literature.

VETMEDIN-CA1 is conditionally approved pending a full demonstration of effectiveness.

Additional information for Conditional Approvals can be found at www.fda.gov/animalca.

A reasonable expectation of effectiveness for VETMEDIN-CA1 is based on results from a multi-site global field study. The study demonstrated a significant delay in the onset of congestive heart failure in dogs with cardiomegaly and heart murmur secondary to Stage B2 MMVD when treated with VETMEDIN-CA1 at the targeted total daily dose of 0.23 mg/lb (0.5 mg/kg) divided into two administrations approximately 12 hours apart.

A total of 363 dogs across various breeds were randomized to treatment. The resulting population evaluated for effectiveness consisted of 353 dogs receiving either pimobendan (VETMEDIN-CA1, n=178) or control product (placebo chewable tablets, n=175).

Dogs ranged between 6 and 17 years of age and weighed between 9 and 33 lbs at enrollment. Dogs were confirmed to have evidence of Stage B2 preclinical MMVD prior to enrollment, including a systolic heart murmur grade of ≥3/6 and evidence of cardiomegaly, including a VHS >10.5, and echocardiographic evidence of LA/Ao ratio ≥1.6 and LVIDDN ≥1.7.

Dogs were ineligible if they were found to have current or previous evidence of cardiogenic pulmonary edema, clinically significant tachyarrhythmias, cardiac disease other than MMVD, significant systemic disease, evidence of pulmonary hypertension (RA:RV gradient > 65 mmHg), were pregnant or lactating female dogs, or if they were treated with prohibited concomitant medications for 14 or more consecutive days.

The primary outcome evaluated was a composite of the development of left-sided CHF or cardiac-related death or euthanasia. Left-sided congestive heart failure was confirmed by radiographic evidence of cardiogenic pulmonary edema. If a dog died in the absence of evidence of a non-cardiac cause of death, prior to radiographic confirmation of pulmonary edema, it was also considered to have reached the primary endpoint. The study was designed to follow individual dogs for up to 3 years or until disease progression into CHF.

At study termination, 41.6% of the dogs in the VETMEDIN-CA1 group had reached the primary endpoint, compared to 50.3% in the control group. The median time to the primary endpoint was 1228 days in the VETMEDIN-CA1 group compared to 761 days in the control group. Thus, administration of VETMEDIN-CA1 to dogs with Stage B2 preclinical MMVD resulted in the prolongation of the preclinical period by 467 days (15.6 months) compared to dogs receiving control product.

Palatability:

In a laboratory study, the palatability of VETMEDIN-CA1 was evaluated in 20 adult female Beagle dogs offered doses twice daily for 14 days. Ninety percent (18 of 20 dogs) voluntarily consumed more than 70% of the 28 tablets offered. Including two dogs that consumed only 4 and 7% of the tablets offered, the average voluntary consumption was 84.2%.

Target Animal Safety:

In a laboratory study, pimobendan chewable tablets were administered to 6 healthy Beagles per treatment group at 0 (control), 1, 3, and 5 times the recommended dosage for 6 months. See the table below for cardiac pathology results. The cardiac pathology/histopathology noted in the 3X and 5X dose groups is typical of positive inotropic and vasodilator drug toxicity in normal dog hearts and is associated with exaggerated hemodynamic responses to these drugs. None of the dogs developed signs of heart failure and there was no mortality.

Incidence of Cardiac Pathology/Histopathology in the Six-month Safety Study

Severe left ventricular hypertrophy with multifocal subendocardial ischemic lesions | One 3X and two 5X dogs a
Moderate to marked myxomatous thickening of the mitral valves | Three 5X dogs
Myxomatous thickening of the chordae tendineae | One 3X and two 5X dogs
Endocardial thickening of the left ventricular outflow tract | One 1X, two 3X and two 5X dogs
Left atrial endocardial thickening (jet lesions) in 2 of the dogs that developed murmurs of mitral valve insufficiency | One 3X and one 5X dog
Granulomatous inflammatory lesion in the right atrial myocardium | One 3X dog

aMost of the gross and histopathologic findings occurred in these three dogs

Murmurs of mitral valve insufficiency were detected in one 3X (Day 65) and two 5X dogs (Days 135 and 163). These murmurs (grades II-III of VI) were not associated with clinical signs.

Indirect blood pressure was unaffected by pimobendan at the label dose (1X). Mean diastolic blood pressure was decreased in the 3X group (74 mmHg) compared to the control group (82 mmHg). Mean systolic blood pressure was decreased in the 5X group (117 mmHg) compared to the control group (124 mmHg). None of the dogs had clinical signs of hypotension.

On 24-hour Holter monitoring, mean heart rate was increased in the 5X group (101 beats/min) compared to the control group (94 beats/min). Not counting escape beats, the 3X and 5X groups had slightly higher numbers of isolated ventricular ectopic complexes (VEs). The maximum number of non-escape VEs recorded either at baseline or in a control group dog was 4 VEs/24 hours. At either Week 4 or Week 20, three 3X group dogs had maximums of 33, 13, and 10 VEs/24 hours, and two 5X group dogs had maximums of 22 and 9 VEs/24 hours. One 1X group dog with no VEs at baseline had 6 VEs/24 hours at Week 4 and again at Week 20. Second-degree atrioventricular heart block was recorded in one 3X group dog at Weeks 4 and 20, and in one dog from each of the 1X and 5X groups at Week 20. None of the dogs had clinical signs associated with these electrocardiogram changes.

Treatment was associated with small differences in mean platelet counts (decreased in the 3X and 1X groups), potassium (increased in the 5X group), glucose (decreased in the 1X and 3X groups), and maximum blood glucose in glucose curves (increased in the 5X group). All individual values for these variables were within the normal range. Three 1X and one 5X group dogs had mild elevations of alkaline phosphatase (less than two times normal).

Loose stools and vomiting were infrequent and self-limiting.

Storage Information:

Store at 20° to 25°C (68° to 77°F), excursions permitted between 15° and 30°C (between 59° and 86°F).

How Supplied:

VETMEDIN®-CA1 (pimobendan) Chewable Tablets:

Available as 1.25 and 5 mg oblong half-scored chewable tablets -

50 tablets per bottle.

NDC 0010-4610-01 - 1.25 mg - 50 tablets

NDC 0010-4612-01 - 5 mg - 50 tablets

References

1 Keene, B., et al. (2019) ACVIM consensus guidelines for the diagnosis and treatment of myxomatous mitral valve disease in dogs. J Vet Intern Med. 33(3):1127-1540.

2 Malcolm, E.L. et. al. (2018) Diagnostic value of vertebral left atrial size as determined from thoracic radiographs for assessment of left atrial size in dogs with myxomatous mitral valve disease. J AM Vet Med Assoc. 253(8):1038-1045.

Marketed by:

Boehringer Ingelheim Animal Health USA Inc.

Duluth, GA 30096

VETMEDIN® is a registered trademark of Boehringer Ingelheim

Vetmedica GmbH used under license.

© 2023 Boehringer Ingelheim Animal Health USA Inc. All rights reserved.

Revised 08/2023

180389-002

Client Information Sheet

This Client Information Sheet contains important information about VETMEDIN-CA1 (pimobendan) Chewable Tablets. You should read this information before you start giving VETMEDIN-CA1 and review it each time the prescription is refilled as there may be new information. This sheet does not take the place of instructions from your veterinarian. Talk with your veterinarian if you do not understand any of this information or if you want to know more about VETMEDIN-CA1.

VETMEDIN-CA1 is conditionally approved by the FDA, and full demonstration of effectiveness (how well the drug works) is dependent on completion of a clinical trial. The use of conditionally approved new animal drugs is limited to a specific use, which can be found on the package insert. Additional information on conditional approval can be found at www.fda.gov/animalca.

Your veterinarian has decided to include VETMEDIN-CA1 as a part of his/her treatment plan for your dog’s heart disease. Be sure to speak with your veterinarian for any questions regarding your dog’s diagnosis or treatment plan.

What is VETMEDIN-CA1 and why has my veterinarian prescribed it?

VETMEDIN-CA1 contains pimobendan which helps the heart to relax and contract (pump) more effectively and it dilates blood vessels which reduces the amount of pressure the heart needs to pump blood.

Your veterinarian has prescribed VETMEDIN-CA1 because your dog has been diagnosed with myxomatous mitral valve disease (MMVD) at a stage known as B2 (see table below). Although your dog does not have any clinical signs of heart disease, VETMEDIN-CA1 can be used to delay the progression of MMVD to heart failure.

MMVD is the most common heart disease in small breed dogs but can also affect larger breeds. Early in MMVD, veterinarians may hear abnormal heart sounds (heart murmurs). MMVD is the primary cause of heart murmurs in older pets. Further testing will be needed to diagnose the stage of the disease and determine if the dog’s heart is enlarged. The table below describes the stages of MMVD and the differences in possible treatments your veterinarian may prescribe.

Description of MMVD Stages and Treatments

Stage | Description | Medical Treatment
B1 | - Abnormal heart sounds (murmurs) can be heard. - The dog’s heart is not enlarged. - There are no outward signs of heart disease. | Medications are not currently recommended.
B2 | - Abnormal heart sounds (murmurs) can be heard. - The dog’s heart is enlarged (sign of disease progression). - There are still no outward signs of heart disease. | VETMEDIN-CA1 is conditionally approved for use in Stage B2.
C/D | Stages C and D means the dog has been diagnosed with congestive heart failure (dog has fluid accumulation in the lungs).; - Abnormal heart sounds (murmurs) can be heard. - The dog’s heart is enlarged. - Outward signs of heart failure can be seen, such as labored breathing, increased resting respiratory rates, fainting, abnormal heart rhythms, and significant coughing. | VETMEDIN is FDA approved for use in dogs diagnosed with congestive heart failure.; Additional medications may also be prescribed to treat the outward signs or to treat the fluid in the dog’s lungs.

Talk to your veterinarian if you have any questions regarding your dog’s heart disease diagnosis.

Is VETMEDIN-CA1 the same as VETMEDIN?

Both products are physically identical and contain the same amount of active ingredient, pimobendan. The differences are the stage of MMVD they are used to treat and their approval status with FDA.

• VETMEDIN-CA1 is conditionally approved by the FDA to delay the onset of congestive heart failure in dogs diagnosed with Stage B2 MMVD. Further testing is being conducted to confirm effectiveness (how well the drug works).

• VETMEDIN is fully approved by the FDA to manage the outward signs of congestive heart failure. VETMEDIN is fully approved because effectiveness in dogs diagnosed with congestive heart failure has already been confirmed and no further testing is required to evaluate how well it works for that use. Talk to your veterinarian if you have any questions about your dog’s heart disease and the use of VETMEDIN-CA1.

What should I tell my veterinarian about my dog before starting VETMEDIN-CA1?

• Tell your veterinarian about other medications your pet is taking, including prescription drugs, over the counter drugs, heartworm preventives, flea & tick products, and vitamins and supplements, including herbal medications.

• Tell your veterinarian if your dog is pregnant, nursing, or you intend to breed him/her.

• Tell your veterinarian if your dog has any other serious health conditions.

• Tell your veterinarian if your dog has or develops any signs of disease progression, such as labored breathing, increased resting respiratory rates, fainting, abnormal heart rhythms, and coughing.

Talk to your veterinarian about the risks and benefits of giving VETMEDIN-CA1 to your dog.

What are some of the possible side effects of VETMEDIN-CA1?

VETMEDIN-CA1 may cause side effects, even at the prescribed dose. Contact your veterinarian immediately if your dog develops a serious or concerning medical problem or side effect while taking VETMEDIN-CA1.

The most common side effects seen in dogs with Stage B2 MMVD while taking VETMEDIN-CA1 Chewable Tablets are cough, vomiting, diarrhea, lethargy (lack of energy), and localized pain (such as in the neck or legs).

Coughing can be a sign that your dog’s heart disease is progressing. Contact your veterinarian if your dog develops worsening coughing or any other sign of disease progression, including labored breathing, increased resting respiratory rates, fainting, and abnormal heart rhythms.

To report suspected adverse reactions (side effects), to obtain a Safety Data Sheet (SDS), or for technical assistance, contact Boehringer Ingelheim Animal Health USA Inc. at 1-888-637-4251. For additional information about reporting adverse drug experiences for animal drugs, contact FDA at 1-888-FDA-VETS or at www.fda.gov/reportanimalae.

How do I give VETMEDIN-CA1 to my dog?

VETMEDIN-CA1 should be given to your dog in their mouth (orally) twice a day, about 12 hours apart. The tablets are scored so that a combination of whole or half tablets may be given to your dog. Because of differences in tablet sizes and dog sizes, the dose you are prescribed to give your dog in the morning may be the same or different from the evening dose. Please give VETMEDIN-CA1 as directed by your veterinarian.

If your dog vomits after being given VETMEDIN-CA1, please contact your veterinarian and unless directed otherwise, do not give additional tablets again until the next scheduled dose.

What if my dog receives more VETMEDIN-CA1 than what is prescribed?

Contact your veterinarian as soon as possible.

What else should I know about VETMEDIN-CA1?

VETMEDIN-CA1 is not for use in humans. Keep this and all medications out of reach of children.

Consult a physician in case of accidental ingestion by humans. It is important to show the treating physician a copy of the package insert, label, or this client information sheet. VETMEDIN-CA1 is a non-sympathomimetic, non-glycoside inotropic drug with vasodilatative properties.

Keep VETMEDIN-CA1 in a secure location out of reach of dogs, cats, and other animals to prevent accidental ingestion or overdose.

This client information sheet contains a summary of important information about VETMEDIN-CA1. For more detailed information about VETMEDIN-CA1, talk with your veterinarian.

Storage Statement: VETMEDIN-CA1 should be stored at room temperatures between 68° to 77°F (20° to 25°C). Temperature as low as 59° F (15°C) and as high as 86°F (30°C) can be acceptable for short periods of time.

Revised 08/2023